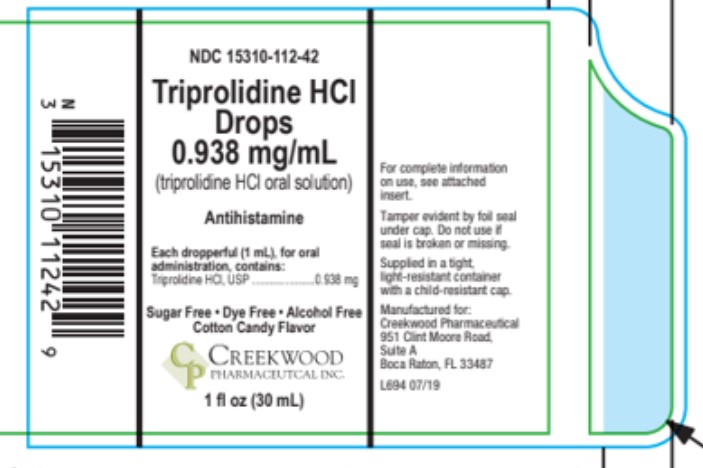 DRUG LABEL: Triprolidine HCl Drops
NDC: 15310-112 | Form: LIQUID
Manufacturer: Creekwood Pharmaceutical Inc.
Category: otc | Type: HUMAN OTC DRUG LABEL
Date: 20211102

ACTIVE INGREDIENTS: TRIPROLIDINE HYDROCHLORIDE 0.938 mg/1 mL
INACTIVE INGREDIENTS: ANHYDROUS CITRIC ACID; GLYCERIN; PROPYLENE GLYCOL; WATER; TRISODIUM CITRATE DIHYDRATE; SACCHARIN SODIUM; SORBITOL

Triprolidine HCL Drops

Other information

Store at 59° - 86°F (15° - 30°C)

Warnings

Do not exceed recommended dosage.

Ask a doctor before use if the child has

- heart disease
- high blood pressure
- thyroid disease
- diabetes
- diffculty in urination due to the enlargement of the prostate gland
- a breathing problem such as emphysema or chronic bronchitis
- glaucoma

Do not use this product

- in a child who is taking a prescription monoamine oxidase inhibitor (MAOI) (certain drugs for depression, psychiatric, or emotional conditions, or Parkinson's disease), or for 2 weeks after stopping the MAOI drug. If you do not know if your child's prescription drug contains an MAOI, ask a doctor or pharmacist before giving this product.

Stop use and ask a doctor if

- nervousness, dizziness, or sleeplessness occur
- symptoms do not improve within 7 days or are accompanies by fever

Keep out of reach of children.

In case of overdose, get medical help or contact a Poison Control Center right away.

Uses

Temporarily relieves these symptoms due to the common cold, hay fever (allergic rhinitis) or other upper respiratory allergies:

- Nasal Congestion
- reduces swelling of nasal passages
- runny nose
- sneezing
- itching of the nose or throat
- itchy,watery eyes

Drug Facts

Active ingredients
(in each 1 mL dropperful)

Triprolidine Hydrochloride 0.938mg

Purpose

Anitihistamine

Directions

Do Not exceed recommended dosage.

Use only with enclosed dropper. Do not use with any other device.

Adults and Children 12 years of age and over | 2.67 mL every 4 hours to 6 hours,not to exceed 4 doses in 24 hours
Children 6 years to under 12 years of age: | 1.33mL every 4 to 6 hours, not to exceed 4 doses in 24 hours
Children under 6 years of age: | Consult a doctor.

Inactive ingredients

Citric Acid, Cotton Candy Flavor, Glycerin, Propylene Glycol, Purified Water, Sodium Citrate, Sodium Saccharin, Sorbitol, Sucralose.

Questions Comments

Seek medical assistance immediately for serious side effects associated with the use of this product. Serious side effects may be reported to this number: 866-991-9870 (mon-Fri 8 a.m to 5 p.m EST)

Product Packaging

The packaging below represents the labeling currently used.
Principal display panel and side panel for 30 mL label:
NDC 15310-112-42

Triprolidine HCl Drops

Alllergic Rhintis, Respiratory Allergies & Nasal Decongestant

Common Cold

Alcohol-Free · Dye Free · Sugar Free · · Cotton Candy Flavor
Each Dropperful (1 mL) contains:

Triprolidine HCl, USP..........................0.938 mg
Net Wt. 1 FL OZ (30 mL)
Tamper evident by foil seal under cap.

Do not use if foil seal is broken or missing.

Manufactured for:

Creekwood Pharmaceutical

951 Clint Moore Road,

Suite A

Boca Taton, FL 33487